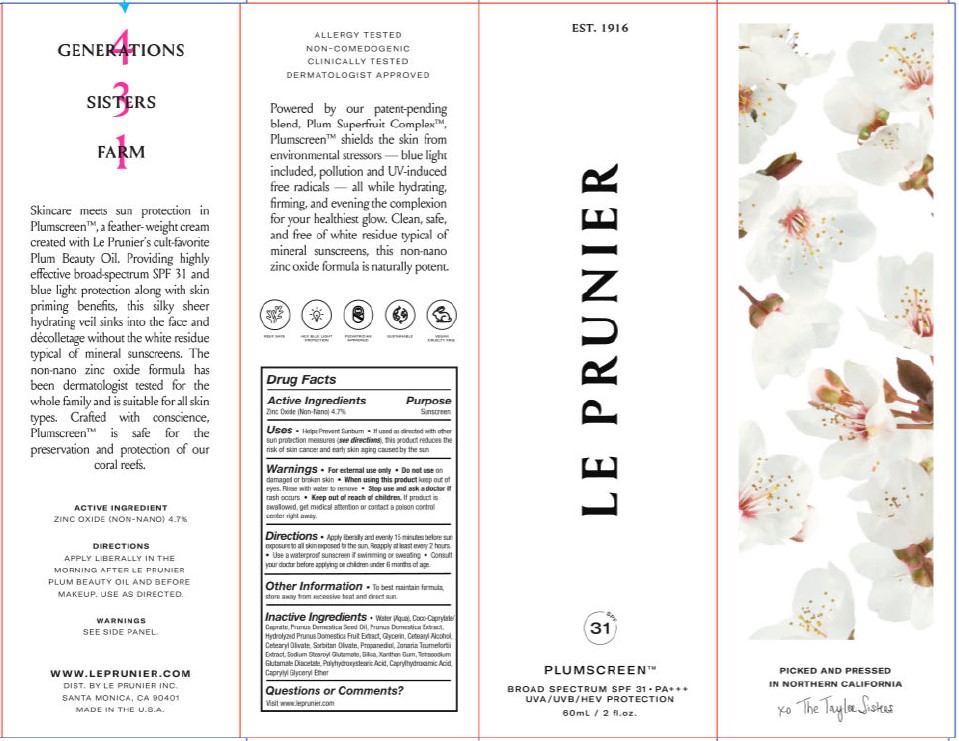 DRUG LABEL: PLUMSCREEN
NDC: 80476-101 | Form: CREAM
Manufacturer: Le Prunier Farms, Inc.
Category: otc | Type: HUMAN OTC DRUG LABEL
Date: 20260107

ACTIVE INGREDIENTS: ZINC OXIDE 4.7 g/100 mL
INACTIVE INGREDIENTS: COCO-CAPRYLATE/CAPRATE; GLYCERIN; PROPANEDIOL; CETOSTEARYL ALCOHOL; POLYHYDROXYSTEARIC ACID (2300 MW); PLUM JUICE; WATER; PLUM SEED OIL; SORBITAN OLIVATE; CETEARYL OLIVATE; TETRASODIUM GLUTAMATE DIACETATE; FUCUS VESICULOSUS; SILICON DIOXIDE; CAPRYLHYDROXAMIC ACID; CAPRYLYL GLYCERYL ETHER; SODIUM STEAROYL GLUTAMATE; XANTHAN GUM

LE PRUNIER - PLUMSCREEN SPF 31 (80476-101)

ACTIVE INGREDIENTS

ZINC OXIDE (NON-NANO) 4.7%

PURPOSE

SUNSCREEN

USES

- HELPS PREVENT SUNBURN
- IF USED AS DIRECTED WITH OTHER SUN PROTECTION MEASURES (SEE DIRECTIONS), THIS PRODUCT REDUCES THE RISK OF SKIN CANCER AND EARLY SKIN AGING CAUSED BY THE SUN

WARNINGS

- FOR EXTERNAL USE ONLY
- DO NOT USE ON DAMAGED OR BROKEN SKIN
- WHEN USING THIS PRODUCT KEEP OUT OF EYES. RINSE WITH WATER TO REMOVE
- STOP USE AND ASK A DOCTOR IF RASH OCCURS

- KEEP OUT OF REACH OF CHILDREN. IF PRODUCT IS SWALLOWED, GET MEDICAL ATTENTION OR CONTACT A POISON CONTROL CENTER RIGHT AWAY.

DIRECTIONS

- APPLY LIBERALLY AND EVENLY 15 MINUTES BEFORE EXPOSURE TO ALL SKIN EXPOSED TO THE SUN. REAPPLY AT LEAST EVERY 2 HOURS.
- USE A WATERPROOF SUNSCREEN IF SWIMMING OR SWEATING
- CONSULT YOUR DOCTOR BEFORE APPLYING ON CHILDREN UNDER 6 MONTHS OF AGE.

OTHER INFORMATION

- TO BEST MAINTAIN FORMULA, STORE AWAY FROM EXCESSIVE HEAT AND DIRECT SUN.

INACTIVE INGREDIENTS

WATER (AQUA), COCO-CAPRYLATE/CAPRATE, PRUNUS DOMESTICA SEED OIL, PRUNUS DOMESTICA EXTRACT, HYDROLYZED PRUNUS DOMESTICA FRUIT EXTRACT, GLYCERIN, CETEARYL ALCOHOL, CETEARYL OLIVATE, SORBITAN OLIVATE, PROPANEDIOL, ZONARIA TOURNEFORTII EXTRACT, SODIUM STEAROYL GLUTAMATE, SILICA, XANTHAN GUM, TETRASODIUM GLUTAMATE DIACETATE, POLYHYDROXYSTEARIC ACID, CAPRYLHYDROXAMIC ACID, CAPRYLYL GLYCERYL ETHER

QUESTIONS?

VISIT WWW.LEPRUNIER.COM